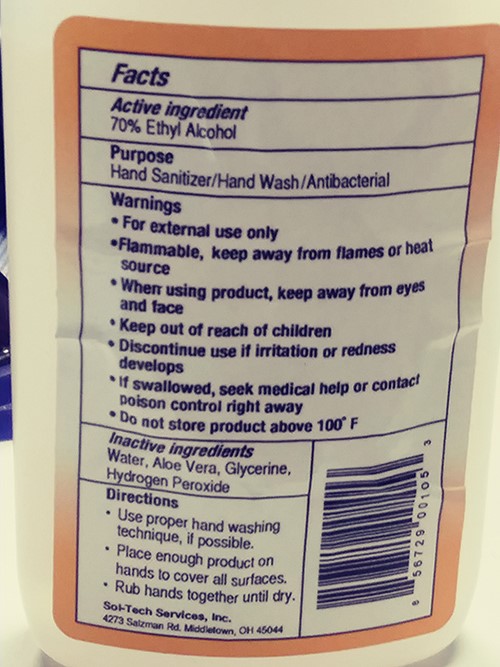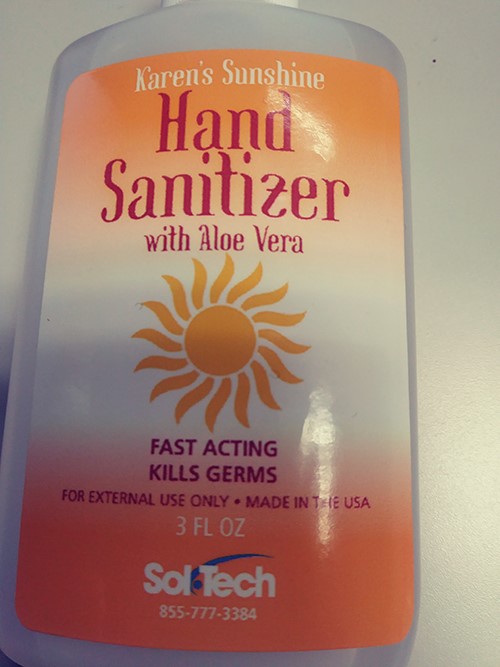 DRUG LABEL: Karens Sunshine
NDC: 79645-402 | Form: LIQUID
Manufacturer: QuickCo, LTD
Category: otc | Type: HUMAN OTC DRUG LABEL
Date: 20200716

ACTIVE INGREDIENTS: ALCOHOL 70 mL/100 mL
INACTIVE INGREDIENTS: HYDROGEN PEROXIDE; ALOE VERA LEAF POLYSACCHARIDES; WATER; GLYCERIN

Active Ingredient

70% Ethyl Alcohol

Purpose

Hand Sanitizer/Hand Wash/Antibacterial

Warnings

- For external use only
- Flammable, keep away from flames or heat source
- When using product, keep away from eyes and face
- Keep out of reach of children
- Discontinue use if irritation or redness develops
- If swallowed, seek medical help or contact poison control right away
- Do not store product above 100º F

Inactive Ingredients

Water, Aloe Vera, Glycerin, Hydrogen Peroxide

Directions

- Use proper hand washing technique, if possible
- Place enough product on hands to cover all surfaces
- Rub hands together until dry

Purpose

Hand Sanitizer/Hand Wash/Antibacterial